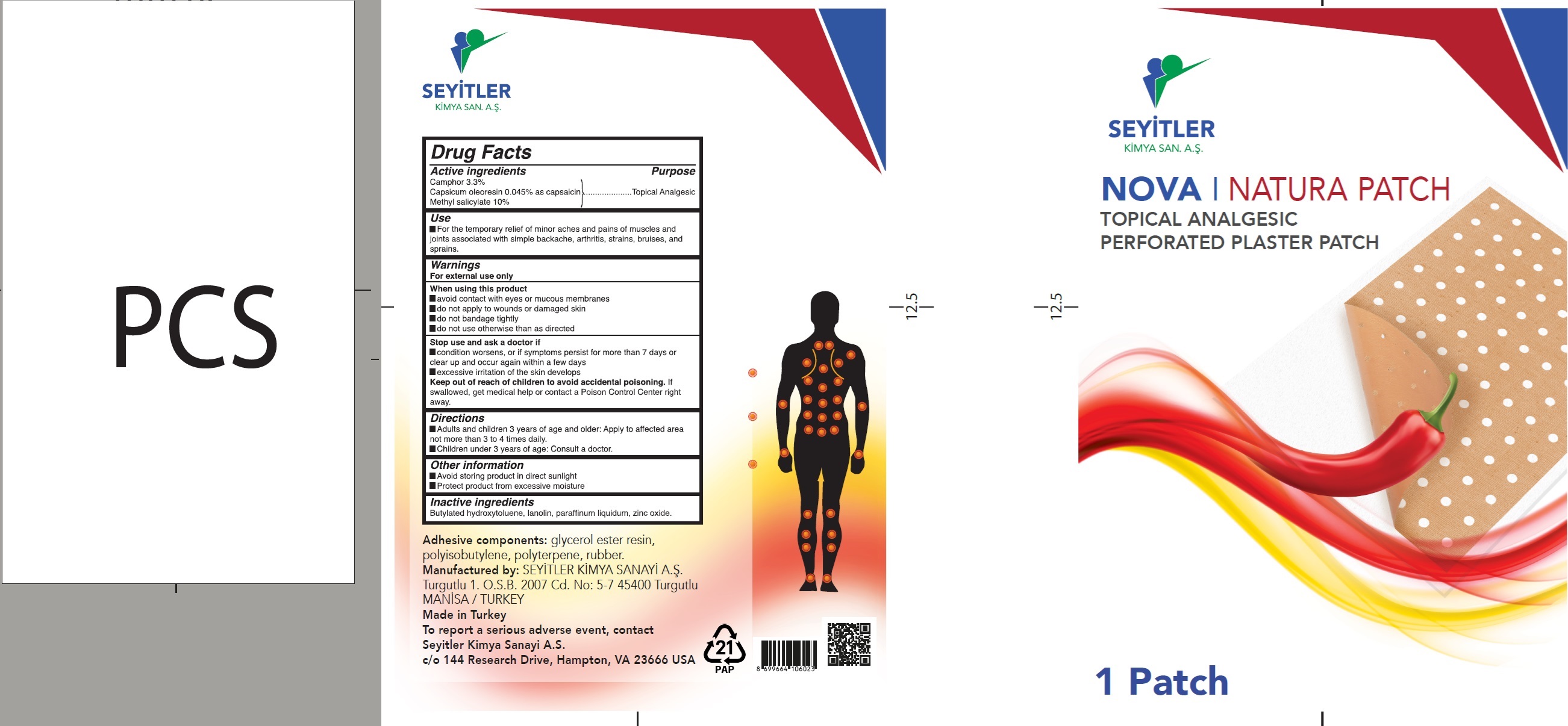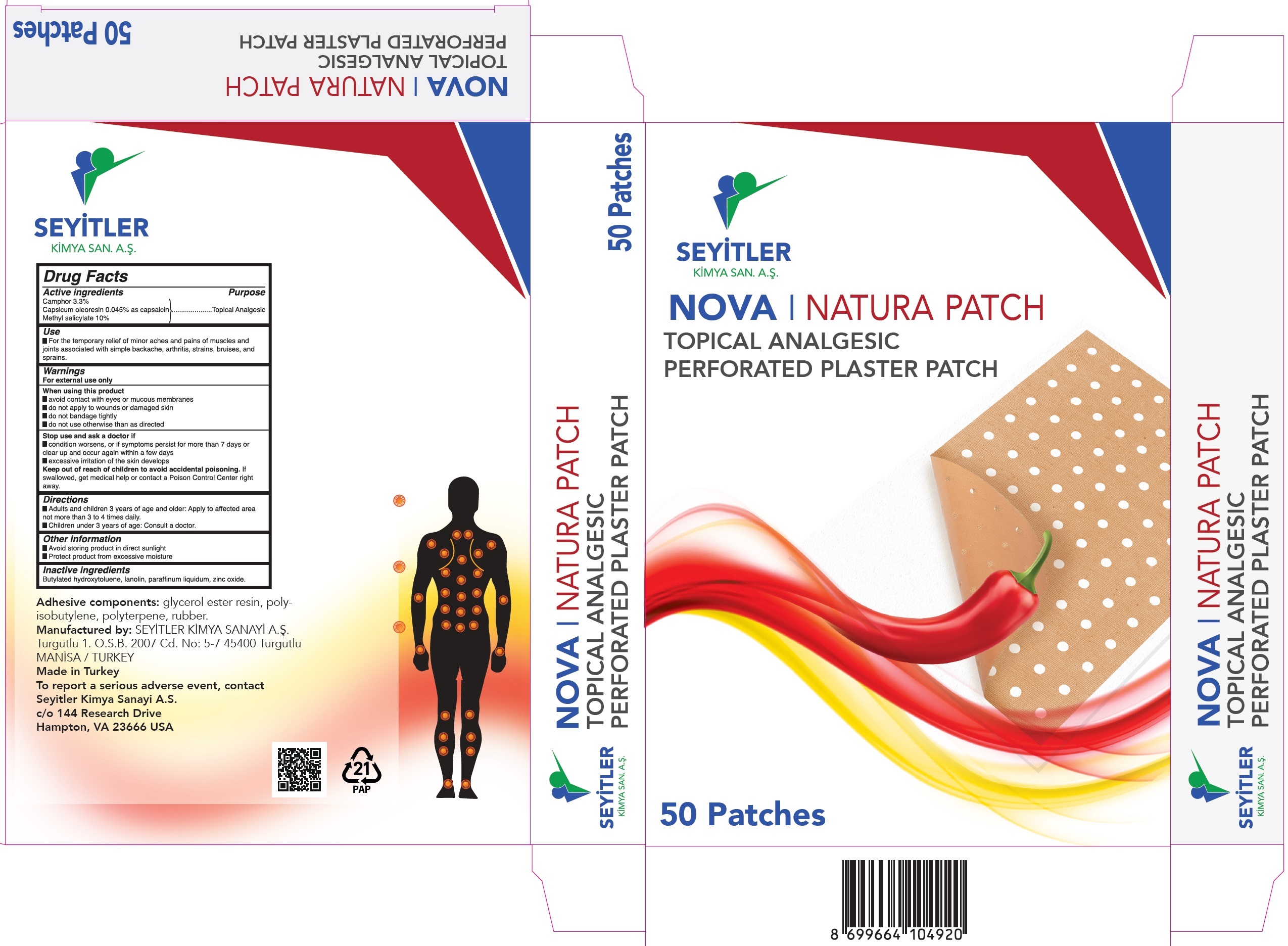 DRUG LABEL: Nova Natura Topical Analgesic
NDC: 84046-001 | Form: PATCH
Manufacturer: SEYITLER KIMYA SANAYI ANONIM SIRKETI
Category: otc | Type: HUMAN OTC DRUG LABEL
Date: 20240206

ACTIVE INGREDIENTS: CAMPHOR (SYNTHETIC) 72.17 mg/1 g; CAPSICUM OLEORESIN 1.01 mg/1 g; METHYL SALICYLATE 218 mg/1 g
INACTIVE INGREDIENTS: BUTYLATED HYDROXYTOLUENE; LANOLIN; MINERAL OIL; ZINC OXIDE

Nova Natura Patch Topical Analgesic

Active ingredients

Camphor 3.3%

Capsicum oleoresin 0.045% as capsaicin

Methyl salicylate 10%

Purpose

Topical Analgesic

Use

- For the temporary relief of minor aches and pains of muscles and joints associated with simple backache, arthritis, strains, bruises, and sprains.

Warnings

For external use only

When using this product

- avoid contact with eyes or mucous membranes
- do not apply to wounds or damaged skin
- do not bandage tightly
- do not use otherwise than as directed

Stop use and ask a doctor if

- condition worsens, or if symptoms persist for more than 7 days or clear up and occur again within a few days
- excessive irritation of the skin develops

Keep out of reach of children to avoid accidental poisoning.

If swallowed, get medical help or contact a Poison Control Center right away.

Directions

- Adults and children 3 years of age and older: Apply to affected area not more than 3 to 4 times daily.
- Children under 3 years of age: Consult a doctor.

Other information

- Avoid storing product in direct sunlight
- Protect product from excessive moisture

Inactive ingredients

Butylated hydroxytoluene, lanolin, paraffinum liquidium, zinc oxide.